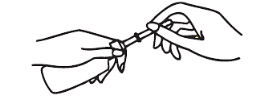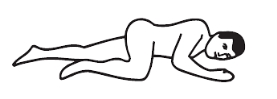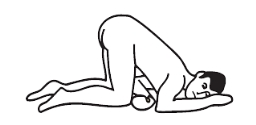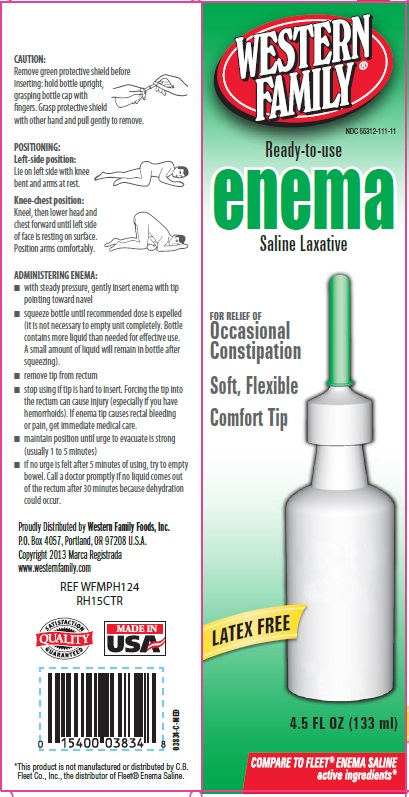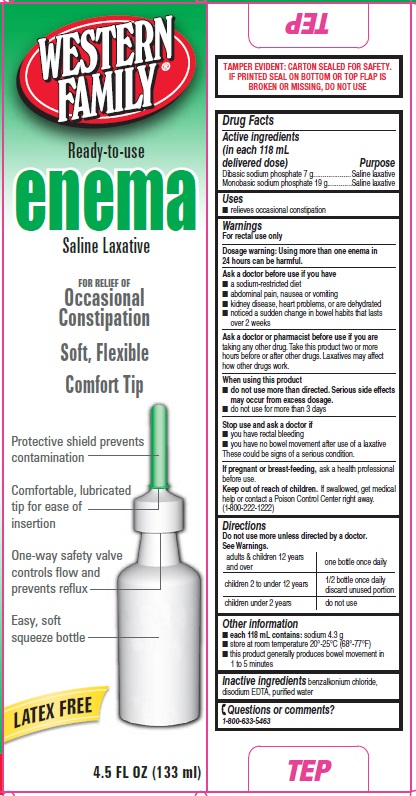 DRUG LABEL: Western Family
NDC: 55312-111 | Form: ENEMA
Manufacturer: WESTERN FAMILY HOLDING COMPANY
Category: otc | Type: HUMAN OTC DRUG LABEL
Date: 20150821

ACTIVE INGREDIENTS: SODIUM PHOSPHATE, DIBASIC 7 g/118 mL; SODIUM PHOSPHATE, MONOBASIC 19 g/118 mL
INACTIVE INGREDIENTS: BENZALKONIUM CHLORIDE; EDETATE DISODIUM; WATER

Active ingredients (in each 118 mL delivered dose)

Dibasic sodium phosphate 7 g

Monobasic sodium phosphate 19 g

Purpose

Saline laxative

Uses

- relieves occasional constipation

Warnings

For rectal use only

Dosage warning: Using more than one enema in 24 hours can be harmful.

Ask a doctor before use if you have

- a sodium-restricted diet
- abdominal pain, nausea or vomiting
- kidney disease, heart problems, or are dehydrated
- noticed a sudden change in bowel habits that lasts over 2 weeks

Ask a doctor or pharmacist before use if you are

taking any other drug. Take this product two or more hours before or after other drugs. Laxatives may affect how other drugs work.

When using this product

- do not use more than directed. Serious side effects may occur from excess dosage.
- do not use for more than 3 days

Stop use and ask a doctor if

- you have rectal bleeding
- you have no bowel movement after use of a laxative

These could be signs of a serious condition.

If pregnant or breast-feeding,

ask a health professional before use.

Keep out of reach of children.

If swallowed, get medical help or contact a Poison Control Center right away. (1-800-222-1222)

Directions

Do not use more unless directed by a doctor. See Warnings.

adults & children 12 years and over | one bottle once daily
children 2 to under 12 years | ½ bottle once daily; Discard unused portion
children under 2 years | do not use

Caution:

REMOVE GREEN PROTECTIVE SHIELD BEFORE INSERTING; HOLD BOTTLE UPRIGHT, GRASPING BOTTLE CAP WITH FINGERS. GRASP PROTECTIVE SHIELD WITH OTHER HAND AND PULL GENTLY TO REMOVE.

Positioning:

Left-side position: Lie on left side with knee bent and arms at rest.

Knee-chest position:

Kneel, then lower head and chest forward until left side of face is resting on surface. Position arms comfortably.

Administering enema:

- With steady pressure, gently insert enema with tip pointing toward navel
- squeeze bottle until recommended dose is expelled (it is not necessary to empty until completely. Bottle contains more liquid than needed for effective use. A small amount of liquid will remain in bottle after squeezing).
- Remove tip from rectum.
- stop using if tip is hard to insert. Forcing the tip into rectum can cause injury (especially if you have hemorrhoids). If enema tip causes rectal bleeding or pain, get immediate medical care.
- maintain position until urge to evacuate is strong (usually 1 to 5 minutes)
- if no urge is felt after 5 minutes of using, try to empty bowel. Call a doctor promptly if no liquid comes out of the rectum after 30 minutes because dehydration could occur.

Other information

- each 118 mL contains: sodium 4.3 g
- store at room temperature 20º-25ºC (68º-77ºF)
- this product generally produces bowel movement in 1 to 5 minutes

Inactive ingredients

benzalkonium chloride, disodium EDTA, purified water

Questions or comments?

1-800-633-5463

Package Label 1 - Principal Display Panel

Western Family

Ready-to-use

Enema

Saline Laxative

For relief of

Occasional Constipation

Soft, Flexible

Comfort Tip

Latex Free

4.5 FL OZ (133 mL)
Compare to Fleet Enema Saline active ingredients*